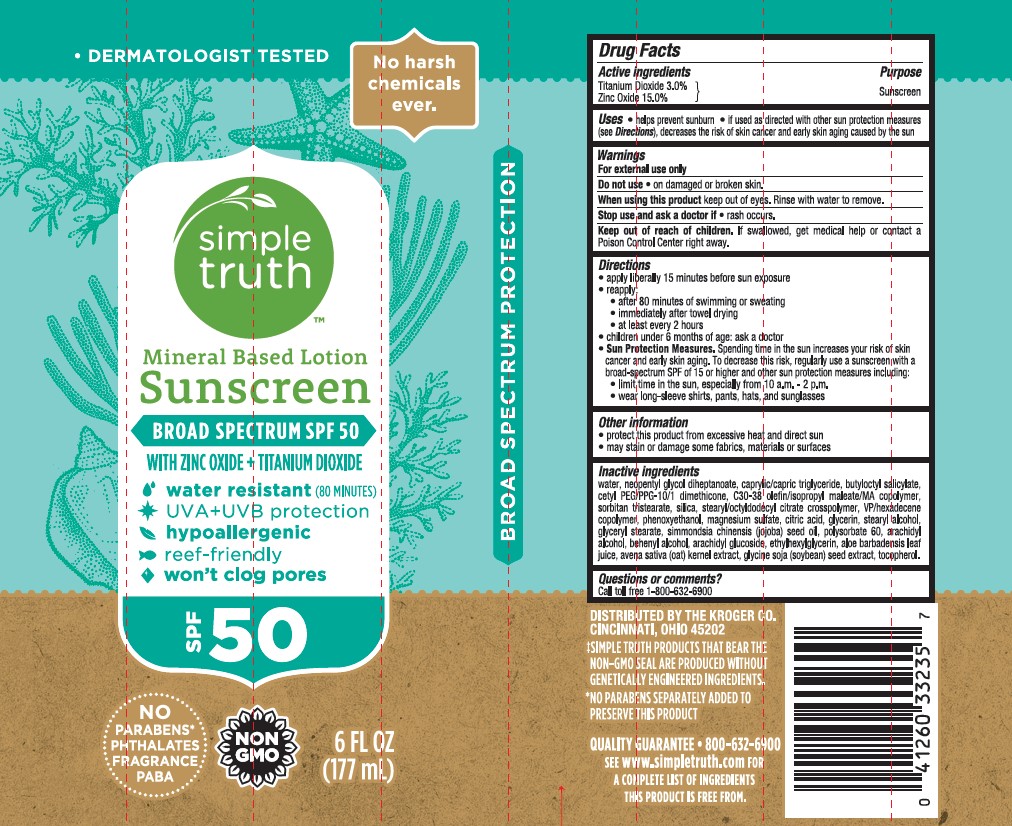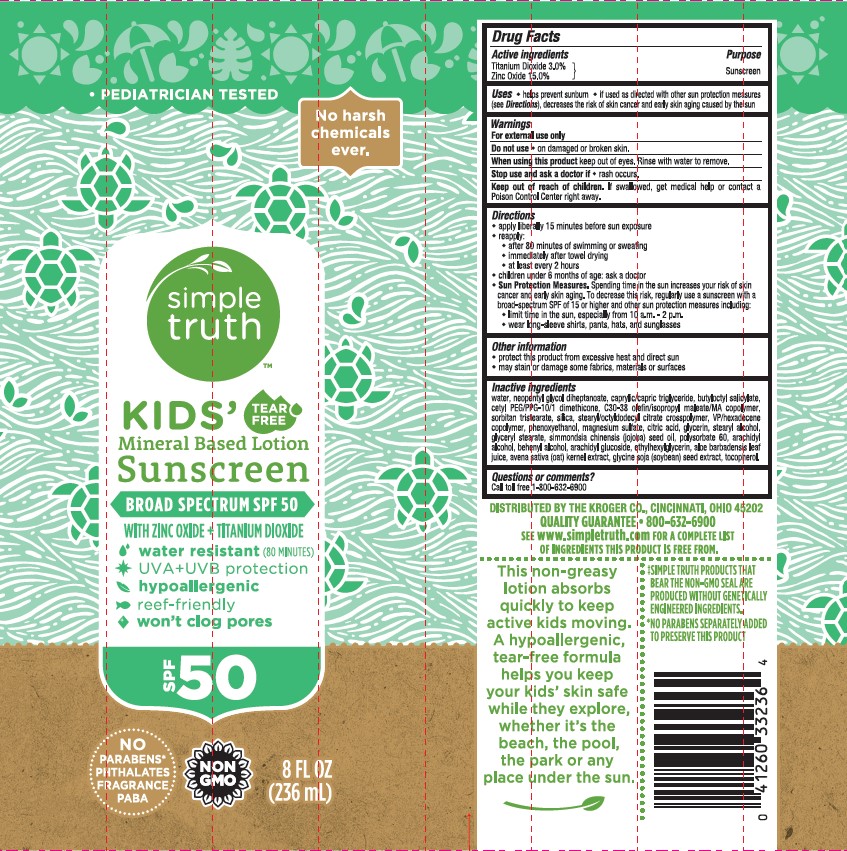 DRUG LABEL: SIMPLE TRUTH MINERAL BASED SPF 50 SUNSCREEN
NDC: 30142-819 | Form: LOTION
Manufacturer: THE KROGER COMPANY
Category: otc | Type: HUMAN OTC DRUG LABEL
Date: 20231026

ACTIVE INGREDIENTS: TITANIUM DIOXIDE 30 mg/1 mL; ZINC OXIDE 150 mg/1 mL
INACTIVE INGREDIENTS: CETYL PEG/PPG-10/1 DIMETHICONE (HLB 5); OAT; JOJOBA OIL; ETHYLHEXYLGLYCERIN; ANHYDROUS CITRIC ACID; WATER; BUTYLOCTYL SALICYLATE; ARACHIDYL GLUCOSIDE; STEARYL ALCOHOL; SORBITAN TRISTEARATE; SILICON DIOXIDE; VINYLPYRROLIDONE/HEXADECENE COPOLYMER; ALOE VERA LEAF; SOYBEAN; ARACHIDYL ALCOHOL; DOCOSANOL; TOCOPHEROL; MAGNESIUM SULFATE HEPTAHYDRATE; GLYCERIN; GLYCERYL 1-STEARATE; POLYSORBATE 60; MEDIUM-CHAIN TRIGLYCERIDES; STEARYL/OCTYLDODECYL CITRATE CROSSPOLYMER; NEOPENTYL GLYCOL DIHEPTANOATE; PHENOXYETHANOL

SIMPLE TRUTH MINERAL BASED SPF 50 SUNSCREEN LOTION

Active ingredients

Titanium Dioxide 3.0%, Zinc Oxide 15.0%

Purpose

Sunscreen

Uses

- helps prevent sunburn
- if used as directed with other sun protection measures (see Directions), decreases the risk of skin cancer and early skin aging caused by the sun

Warnings

For external use only

Do not use

- on damaged or broken skin.

When using this product

keep out of eyes. Rinse with water to remove.

Stop use and ask a doctor if

- rash occurs.

Keep out of reach of children.

If swallowed, get medical help or contact a Poison Control Center right away.

Directions

- apply liberally 15 minutes before sun exposure

- reapply:
- after 80 minutes of swimming or sweating
- immediately after towel drying
- at least every 2 hours

- children under 6 months of age: Ask a doctor

- Sun Protection Measures. Spending time in the sun increases your risk of skin cancer and early skin aging. To decrease this risk, regularly use a sunscreen with a Broad Spectrum SPF value of 15 or higher and other sun protection measures including:
- limit time in the sun, especially from 10 a.m.-2 p.m.
- wear long-sleeved shirts, pants, hats, and sunglasses

Other information

- protect the product in this container from excessive heat and direct sun
- may stain or damage some fabrics, materials or surfaces

Inactive ingredients

water, neopentyl glycol diheptanoate, caprylic/capric triglyceride, butyloctyl salicylate, cetyl PEG/PPG-10/1 dimethicone, C30-38 olefin/isopropyl maleate/ MA copolymer, sorbitan tristearate, silica, stearyl/octyldodecyl citrate crosspolymer, VP/hexadecene copolymer, phenoxyethanol, magnesium sulfate, citric acid, glycerin, stearyl alcohol, glyceryl stearate, simmondsia chinensis (jojoba) seed oil, polysorbate 60, arachidyl alcohol, behenyl alcohol, arachidyl glucoside, ethylhexylglycerin, aloe barbadensis leaf juice, avena sativa (oat) kernel extract, glycine soja (soybean) seed extract, tocopherol.